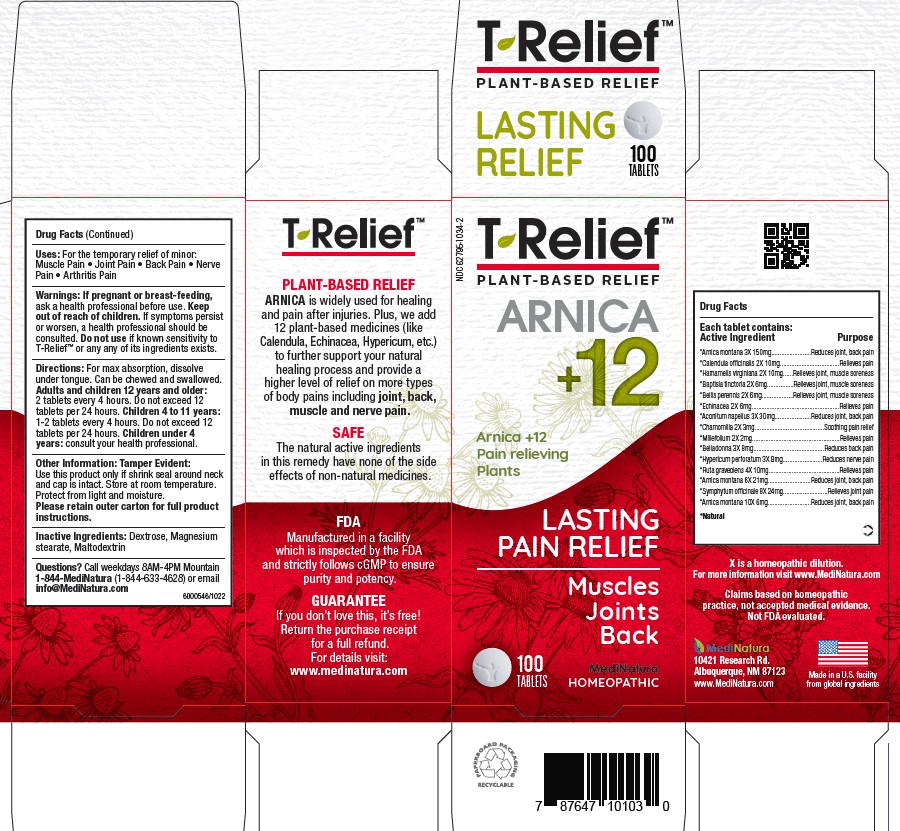 DRUG LABEL: T-Relief
NDC: 62795-1034 | Form: TABLET, CHEWABLE
Manufacturer: MediNatura Inc
Category: homeopathic | Type: HUMAN OTC DRUG LABEL
Date: 20230321

ACTIVE INGREDIENTS: ACONITUM NAPELLUS 3 [hp_M]/1 1; MATRICARIA RECUTITA 2 [hp_X]/1 1; HAMAMELIS VIRGINIANA ROOT BARK/STEM BARK 2 [hp_X]/1 1; HYPERICUM PERFORATUM 3 [hp_X]/1 1; RUTA GRAVEOLENS FLOWERING TOP 4 [hp_X]/1 1; COMFREY ROOT 8 [hp_X]/1 1; BAPTISIA TINCTORIA ROOT 2 [hp_X]/1 1; ATROPA BELLADONNA 3 [hp_X]/1 1; BELLIS PERENNIS 2 [hp_X]/1 1; CALENDULA OFFICINALIS FLOWERING TOP 2 [hp_X]/1 1; ECHINACEA ANGUSTIFOLIA 2 [hp_X]/1 1; ARNICA MONTANA 3 [hp_X]/1 1; ACHILLEA MILLEFOLIUM WHOLE 2 [hp_X]/1 1
INACTIVE INGREDIENTS: MAGNESIUM STEARATE 1 kg/1 1; LACTOSE MONOHYDRATE 99 kg/1 1; DEXTROSE; MALTODEXTRIN

T-Relief Tablet

Uses

For the temporary relief of minor: Muscle Pain, joint pain, back pain, nerve pain and Arthritis pain

WARNINGS

If pregnant or breast-feeding ask a heath professional before use. Keep out of reach of children. If symptoms persist or worsen, a health professional should be consulted. Do not use if known sensitivity to T-Relief ™ or any of its ingredients exists

DIRECTIONS

For max absorption, dissolve under tongue. Can be chewed and swallowed. Adults and children 12 years and older: 2 tablets every 4 hours. Do not exceed 12 tablets per 24 hours. Children 4 to 11years: Chew 1-2 tablets every 4 hours. Do not exceed 12 per 24 hours.

Children under 4 years, consult your health professional.

INACTIVE INGREDIENTS

Dextrose, Maltodextrin and Magnesium Stearate

KEEP OUT OF REACH OF CHILDREN

Purpose

Relieves Pain:

Joint Pain
Back Pain
Muscular Pain

ACTIVE INGREDIENTS

Each tablet contains: *Arnica
montana 3X 150mg, *Calendula officinalis 2X 10mg,
*Hamamelis virginiana 2X 10mg, *Baptisia tinctoria
2X 6mg, *Bellis perennis 2X 6mg, *Echinacea 2X 6mg,
*Aconitum napellus 3X 30mg, *Chamomilla 2X 3mg,
*Millefolium 2X 2mg, *Belladonna 3X 8mg, *Hypericum
perforatum 3X 8mg, *Ruta graveolens 4X 10mg,
*Arnica montana 6X 21mg, *Symphytum officinale 8X
24mg, *Arnica montana 10X 6mg. *Natural

PACKAGE LABEL

Add image transcription here...